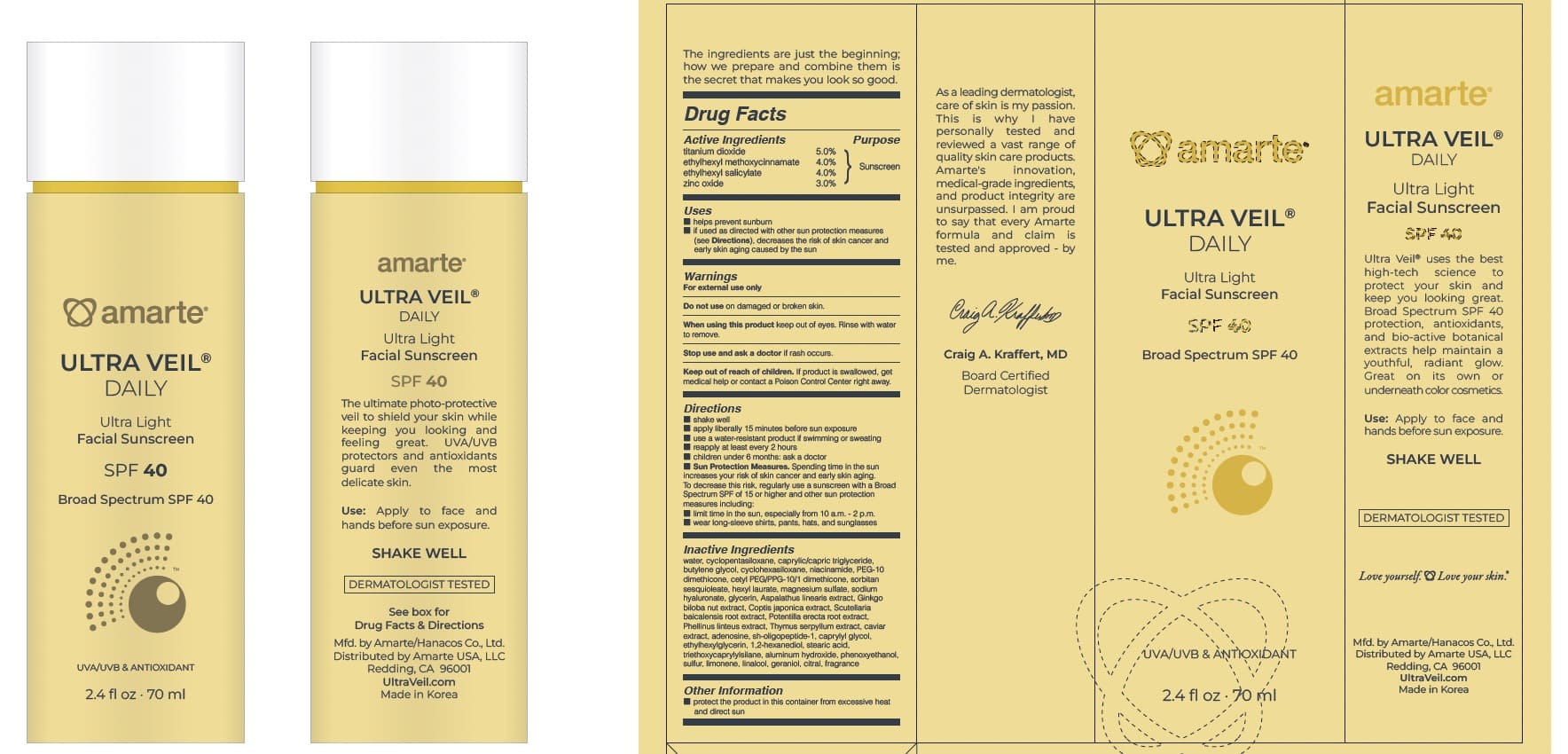 DRUG LABEL: Amarte ULTRA VEIL Daily
NDC: 84779-115 | Form: LOTION
Manufacturer: Amarte USA LLC
Category: otc | Type: HUMAN OTC DRUG LABEL
Date: 20250715

ACTIVE INGREDIENTS: TITANIUM DIOXIDE 50 mg/1 mL; ZINC OXIDE 30 mg/1 mL; ETHYLHEXYL SALICYLATE 40 mg/1 mL; ETHYLHEXYL METHOXYCINNAMATE 40 mg/1 mL
INACTIVE INGREDIENTS: MEDIUM-CHAIN TRIGLYCERIDES; SODIUM HYALURONATE; GLYCERIN; SCUTELLARIA BAICALENSIS ROOT; 1,2-HEXANEDIOL; PEG-10 DIMETHICONE (600 CST); WATER; PHELLINUS LINTEUS WHOLE; BUTYLENE GLYCOL; THYMUS SERPYLLUM; CAVIAR, UNSPECIFIED; CAPRYLYL GLYCOL; CITRAL; CETYL PEG/PPG-10/1 DIMETHICONE (HLB 2); CYCLOMETHICONE 5; CYCLOHEXASILOXANE; NIACINAMIDE; SORBITAN SESQUIOLEATE; HEXYL LAURATE; ASPALATHUS LINEARIS WHOLE; GINKGO BILOBA SEED; ETHYLHEXYLGLYCERIN; TRIETHOXYCAPRYLYLSILANE; LINALOOL; PHENOXYETHANOL; SULFUR; GERANIOL; MAGNESIUM SULFATE, UNSPECIFIED; STEARIC ACID; ADENOSINE; COPTIS JAPONICA WHOLE; POTENTILLA ERECTA ROOT; SH-OLIGOPEPTIDE-1; ALUMINUM HYDROXIDE; LIMONENE, (+)-

Amarte-Hanacos Sunscreen Base Color 70 mL

Active Ingredient(s)

titanium dioxide 5.0%

ethylhexyl methoxycinnamate 4.0%

ethylhexyl salicylate 4.0%

zinc oxide 3.0%

Purpose

Sunscreen

Use

■ helps prevent sunburn ■ if used as directed with other sun protection measures (see Directions), decreases the risk of skin cancer and early skin aging caused by the sun

Warnings

For external use only
Do not use on damaged or broken skin.
When using this product keep out of eyes. Rinse with water to remove.
Stop use and ask a doctor if rash occurs.
Keep out of reach of children. If product is swallowed, get medical help or contact a Poison Control Center right away.

WHEN USING

keep out of eyes. Rinse with water to remove.

KEEP OUT OF REACH OF CHILDREN

If product is swallowed, get medical help or contact a Poison Control Center right away.

Directions

Directions ■ shake well ■ apply liberally 15 minutes before sun exposure ■ use a water-resistant product if swimming or sweating ■ reapply at least every 2 hours ■ children under 6 months: ask a doctor ■ Sun Protection Measures. Spending time in the sun increases your risk of skin cancer and early skin aging. To decrease this risk, regularly use a sunscreen with a Broad Spectrum SPF of 15 or higher and other sun protection measures including: ■ limit time in the sun, especially from 10 a.m. - 2 p.m. ■ wear long-sleeve shirts, pants, hats, and sunglasses

Inactive ingredients

water, cyclopentasiloxane, caprylic/capric triglyceride, butylene glycol, cyclohexasiloxane, niacinamide, PEG-10 dimethicone, cetyl PEG/PPG-10/1 dimethicone, sorbitan sesquioleate, hexyl laurate, magnesium sulfate, sodium hyaluronate, glycerin, Aspalathus linearis extract, Ginkgo biloba nut extract, Coptis japonica extract, Scutellaria baicalensis root extract, Potentilla erecta root extract, Phellinus linteus extract, Thymus serpyllum extract, caviar extract, adenosine, sh-oligopeptide-1, caprylyl glycol, ethylhexylglycerin, 1,2-hexanediol, stearic acid, triethoxycaprylylsilane, aluminum hydroxide, phenoxyethanol, sulfur, limonene, linalool, geraniol, citral, fragrance

Other information

■ protect the product in this container from excessive heat and direct sun